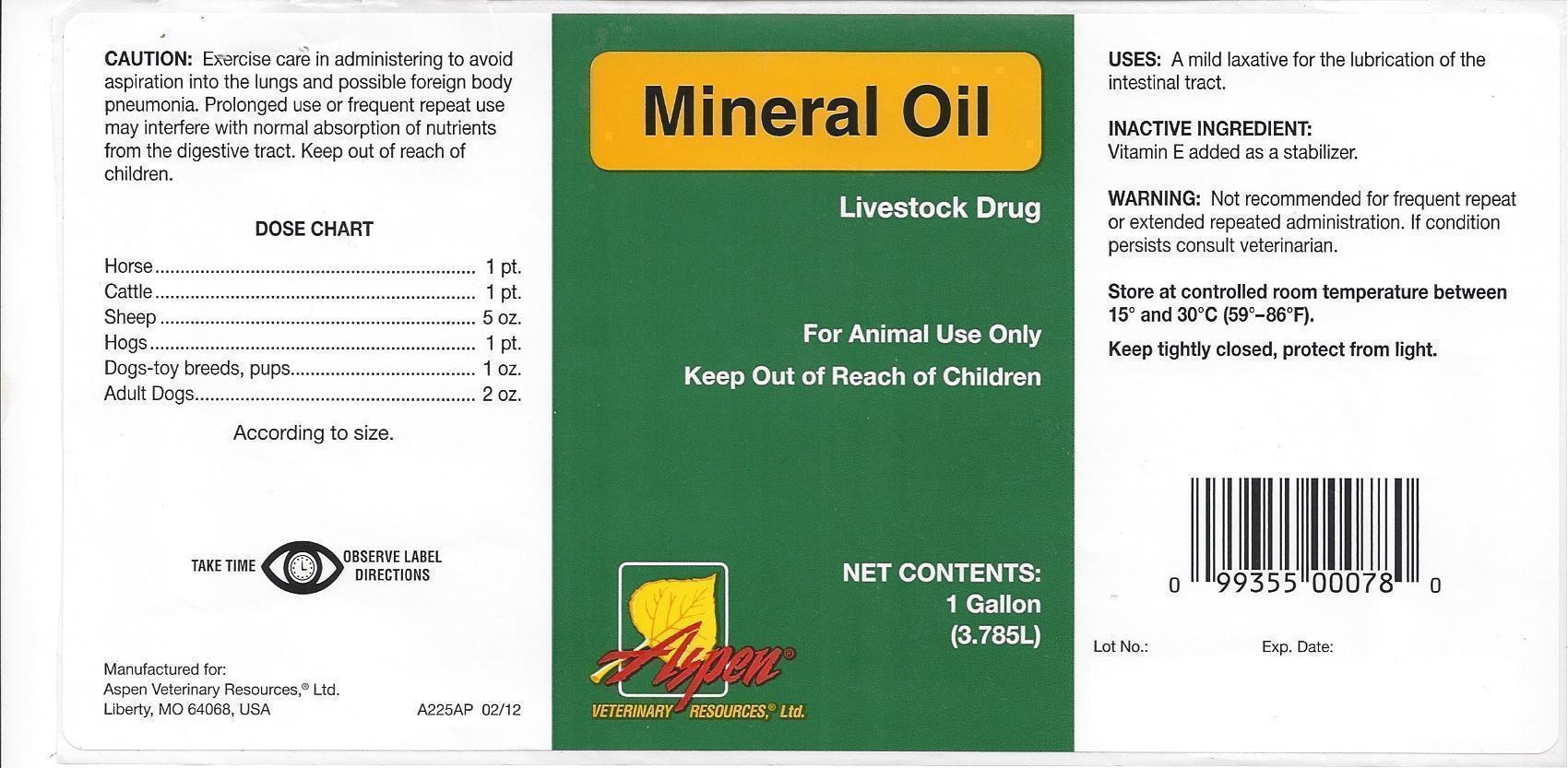 DRUG LABEL: MINERAL OIL LIGHT
NDC: 46066-003 | Form: LIQUID
Manufacturer: ASPEN VETERINARY
Category: animal | Type: OTC ANIMAL DRUG LABEL
Date: 20130917

ACTIVE INGREDIENTS: LIGHT MINERAL OIL 3.45 kg/3.45 kg

ASPEN VETERINARY MINERAL OIL

Mineral Oil

Livestock Drug

For Animal Use Only

Keep Out of Reach of Children

NET CONTENTS:

1 Gallon

(3.785L)

Aspen

Veterinary Resources, Ltd.

CAUTION:

Excercise care in administering to avoid aspiration into the lungs and possible foreign body pneumonia. Prolonged use or frequent repeat use may interfere with normal absorption of nutrients from the digestive tract. Keep out of reach of children.

DOSE CHART

Horse…………………………………………1 pt.

Cattle…………………………………………1 pt..

Sheep…………………………………….….5 oz.

Hogs…………………………………….…….1 pt.

Dogs-toy breeds, pups.............1 oz.

Adult dogs.………………………….…...2 oz.

According to size.

TAKE TIME OBSERVE LABEL DIRECTIONS

Manufactured for:

Aspen Veterinary Resources, Ltd.

Liberty, MO 64068, USA A225AP 02/12

USES:

A mild laxative for the lubrication of the intestinal tract.

INACTIVE INGREDIENT:

Vitamin E added as a stabilizer.

WARNING:

Not recommended for frequent repeat or extended repeated administration. If condition persists consult veterinarian.

STORAGE AND HANDLING

Store at controlled room temperature between 15º AND 30ºC (59ºF-86ºF).

Keep tightly closed, protect from light.

Lot No.: Exp. Date: